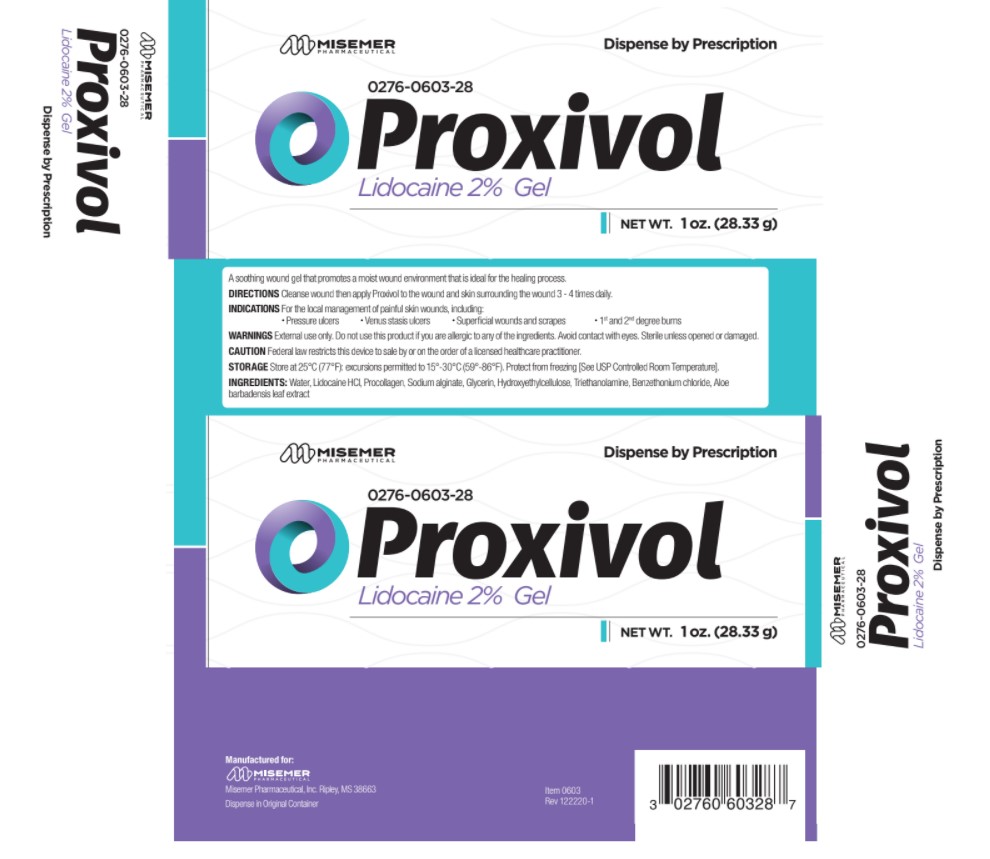 DRUG LABEL: Proxivol
NDC: 0276-0603
Manufacturer: Misemer Pharmaceutical
Category: other | Type: PRESCRIPTION MEDICAL DEVICE LABEL
Date: 20220201
INACTIVE INGREDIENTS: WATER; LIDOCAINE HYDROCHLORIDE; BOVINE TYPE I COLLAGEN; ALOE VERA LEAF; SODIUM ALGINATE; GLYCERIN; HYDROXYETHYL CELLULOSE (100 MPA.S AT 2%); TROLAMINE; BENZETHONIUM CHLORIDE

Proxivol

Proxivol is a soothing wound gel that promotes a moist wound environment that is ideal for the healing process.

Directions:

Cleanse wound then apply Proxivol to the wound and skin surrounding the wound 3 - 4 times daily.

Indications:

For the local management of painful skin wounds, including:
• Pressure ulcers
• Venus stasis ulcers
• Superficial wounds and scrapes
• 1st and 2nd degree burns

Warnings:

External use only. Do not use this product if you are allergic to any of the ingredients. Avoid contact with eyes. Sterile unless opened or damaged.

Caution:

Federal law restricts this device to sale by or on the order of a licensed healthcare practitioner.

Storage:

Store at 25°C (77°F): excursions permitted to 15°-30°C (59°-86°F). Protect from freezing [See USP Controlled Room Temperature].

Ingredients:

Water, Lidocaine HCl, Collagen, Aloe Vera gel, Sodium alginate, Glycerin, Hydroxyethylcellulose, Triethanolamine, Benzethonium chloride.

Call your doctor about side effects. You may report side effects to Misemer Pharmaceutical at 1-662-993-9625 or the FDA at 1-800-FDA-1088.

How Supplied:

Proxivol wound gel is supplied as a gel in:
1 oz. (28.33g) tube, NDC 0276-0603-28

Distributed By:
Misemer Pharmaceutical
Ripley, MS 38663

Item 0603

Rev 1021